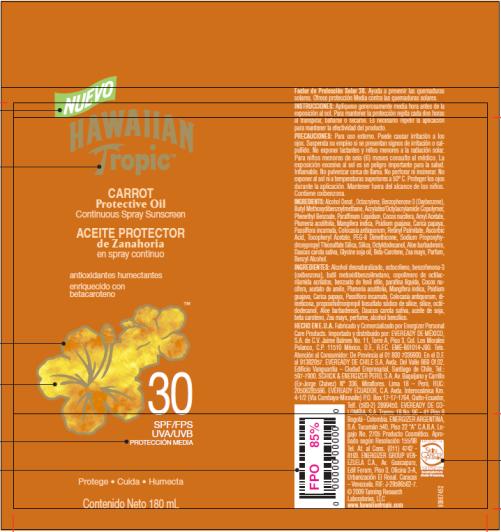 DRUG LABEL: Hawaiian Tropic Carrot Protective Oil SPF 30
NDC: 17630-2039 | Form: OIL
Manufacturer: Accra-Pac, Inc.
Category: otc | Type: HUMAN OTC DRUG LABEL
Date: 20100328

ACTIVE INGREDIENTS: OCTOCRYLENE 0.077 mL/1 mL; OXYBENZONE 0.03 mL/1 mL; AVOBENZONE 0.02 mL/1 mL
INACTIVE INGREDIENTS: MINERAL OIL; AMYL ACETATE; GUAVA; PASSIFLORA INCARNATA TOP; VITAMIN A PALMITATE; ASCORBIC ACID; .ALPHA.-TOCOPHEROL ACETATE, D-; SILICON DIOXIDE; OCTYLDODECANOL; CARROT; SOYBEAN; BETA CAROTENE; BENZYL ALCOHOL; COCONUT OIL; PLUMERIA EXTRACT; MANGO; ALOE VERA LEAF; CORN OIL

Hawaiian Tropic Carrot Protective Oil SPF 30

Active Ingredients

Octocrylene 0.077mL / 1mL

Oxybenzone 0.03mL / 1mL

Avobenzone 0.02mL / 1mL

INSTRUCCIONES:

Aplíquese generosamente media hora antes de la exposición al sol. Para mantener la protección repita cada dos horas al transpirar, bañarse o secarse. Es necesario repetir la aplicación para mantener la efectividad del producto.

PRECAUCIONES:

Para uso externo. Puede causar irritación a los ojos. Suspenda su empleo si se presentan signos de irritación o salpullido. No exponer lactantes y niños menores a la radiación solar. Para niños menores de seis (6) meses consulte al médico. La exposición excesiva al sol es un peligro importante para la salud. Inflamable. No pulverizar cerca de llama. No perforar ni incinerar. No exponer al sol ni a temperaturas superiores a 50° C. Proteger los ojos durante la aplicación. Mantener fuera del alcance de los niños. Contiene oxibenzona.

INGREDIENTS:

Alcohol Denat., Octocrylene, Benzophenone-3 (Oxybenzone), Butyl Methoxydibenzoylmethane, Acrylates/Octylacrylamide Copolymer, Phenethyl Benzoate, Paraffinum Liquidum, Cocos nucifera, Amyl Acetate, Plumeria acutifolia, Mangifera indica, Psidium guajava, Carica papaya, Passiflora incarnata, Colocasia antiquorum, Retinyl Palmitate, Ascorbic Acid, Tocopheryl Acetate, PEG-8 Dimethicone, Sodium Propoxyhydroxypropyl Thiosulfate Silica, Silica, Octyldodecanol, Aloe barbadensis, Daucus carota sativa, Glycine soja oil, Beta-Carotene, Zea mays, Parfum, Benzyl Alcohol.

INGREDIENTES:

Alcohol desnaturalizado, octocrileno, benzofenona-3 (oxibenzona), butil metoxidibenzoilmetano, copolímero de octilacrilamida acrilatos, benzoato de fenil etilo, parafina líquida, Cocos nucifera, acetato de amilo, Plumeria acutifolia, Mangifera indica, Psidium guajava, Carica papaya, Passiflora incarnata, Colocasia antiquorum, dimeticona, propoxihidroxipropil tiosulfato sódico de sílice, sílice, octildodecanol, Aloe barbadensis, Daucus carota sativa, aceite de soja, beta caroteno, Zea mays, perfume, alcohol bencílico.

HECHO EN E.U.A. Fabricado y Comercializado por Energizer Personal Care Products. Importado y distribuido por: EVEREADY DE MÉXICO, S.A. de C.V. Jaime Balmes No. 11, Torre A, Piso 3, Col. Los Morales Polanco, C.P. 11510 México, D.F., R.F.C. EME-861014-J90. Tels. Atención al Consumidor: De Provincia al 01 800 7039900. En el D.F. al 91382057. EVEREADY DE CHILE S.A. Avda. Del Valle 869 Of.02. Edificio Vanguardia – Ciudad Empresarial, Santiago de Chile, Tel.: 597-7900. SCHICK & ENERGIZER PERÚ, S.A. Av. Baquíjano y Carrillo (Ex-Jorge Chávez) N° 336, Miraflores. Lima 18 – Perú. RUC: 20506285586. EVEREADY ECUADOR, C.A. Avda. Interoceánica Km. 4-1/2 (Vía Cumbaya-Miravalle) P.O. Box 17-17-1764, Quito-Ecuador, Telf. (593-2) 2899450. EVEREADY DE COLOMBIA, S.A. Transv. 18 No. 96 – 41 Piso 8 Bogotá - Colombia. ENERGIZER ARGENTINA, S.A. Tucumán 540, Piso 22 “A” C.A.B.A. Legajo No. 2705 Producto Cosmético. Aprobado según Resolución 155/98 Tel. At. al Cons. (011) 4742 - 8193. ENERGIZER GROUP VENEZUELA C.A., Av. Guaicaipuro, Edif Forum, Piso 3, Oficina 3-A, Urbanización El Rosal. Caracas – Venezuela. RIF: J-29586562-7.

© 2009 Tanning Research
Laboratories, LLC
www.hawaiiantropic.com

PRINCIPAL DISPLAY PANEL

NUEVO
HAWAIIAN
Tropic TM
CARROT
Protective Oil
Continuous Spray Sunscreen
ACEITE PROTECTOR
de Zanahoria
en spray continuo
antioxidants humectantes
enriquecido con
betacaroteno
30
SPF/FPS
UVA/UVB
PROTECCIÓN MEDIA
Protege Cuida Humecta
Contenido Neto 180 mL